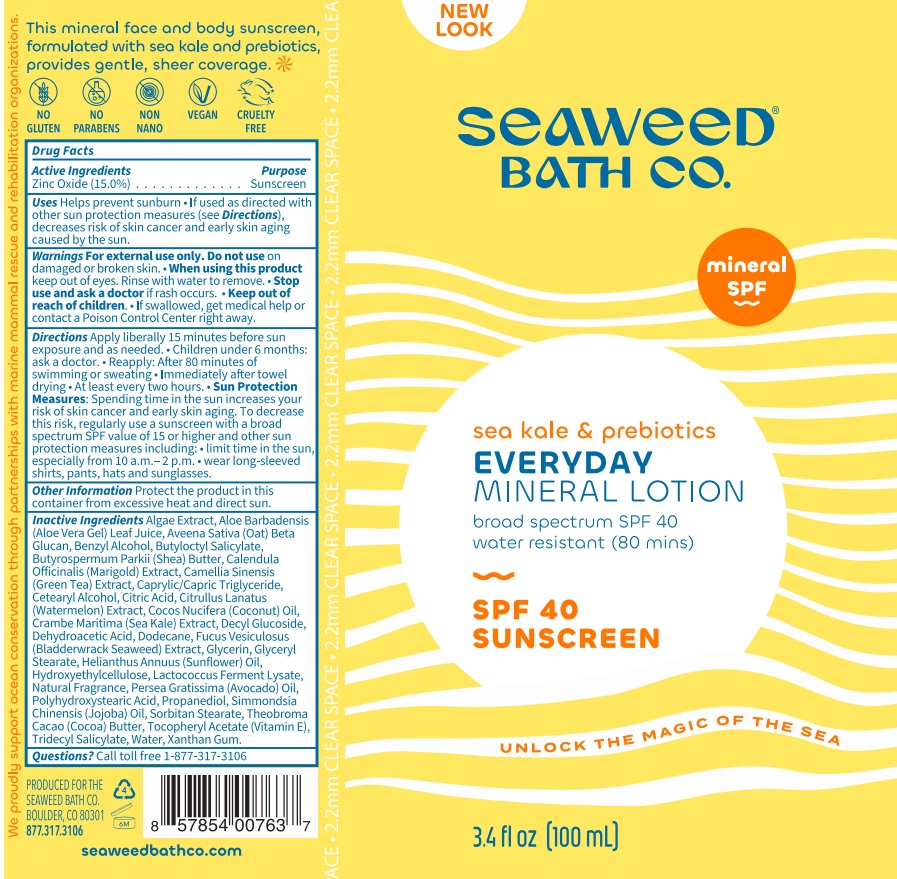 DRUG LABEL: SEAWEED BATH CO Everyday Mineral SPF 40
NDC: 81159-259 | Form: LOTION
Manufacturer: The Seaweed Bath Co.
Category: otc | Type: HUMAN OTC DRUG LABEL
Date: 20240626

ACTIVE INGREDIENTS: ZINC OXIDE 150 mg/1 mL
INACTIVE INGREDIENTS: ALOE VERA LEAF; BENZYL ALCOHOL; BUTYLOCTYL SALICYLATE; SHEA BUTTER; CALENDULA OFFICINALIS FLOWER; GREEN TEA LEAF; MEDIUM-CHAIN TRIGLYCERIDES; CETOSTEARYL ALCOHOL; CITRIC ACID MONOHYDRATE; WATERMELON; COCONUT OIL; DECYL GLUCOSIDE; DEHYDROACETIC ACID; DODECANE; FUCUS VESICULOSUS; GLYCERIN; GLYCERYL MONOSTEARATE; HELIANTHUS ANNUUS FLOWERING TOP; HYDROXYETHYL CELLULOSE, UNSPECIFIED; AVOCADO OIL; JOJOBA OIL; PROPANEDIOL; SORBITAN MONOSTEARATE; COCOA; .ALPHA.-TOCOPHEROL ACETATE; TRIDECYL SALICYLATE; WATER; XANTHAN GUM

SEAWEED BATH CO. Everyday Mineral SPF-40 Lotion

Active Ingredient

Zinc Oxide 15.0%

Purpose

Sunscreen

Uses:

- Helps prevent sunburn
- Higher SPF gives more sunburn protection
- Retains SPF after 80 minutes of swimming or sweating.

Warnings:

For external use only.

Do not use

on damaged or broken skin.

When using this product

- keep out of eyes. Rinse with water to remove.

Stop use and ask a doctor

- ir rash occurs.

Keep out of reach of children.

- If swallowed, get medical help or contact a Poison Control Center right away.

Directions:

- Apply liberally 15 minutes before sun exposure and as needed.
- Children under 6 months: ask a doctor.
- Reapply:
- After 80 minutes of swimming or sweating
- Immediately after towel drying
- At least every two hours.
- Spending time in the sun increases your risk of skin cancer and early skin aging. To decrease this risk, regularly use a sunscreen with a broad spectrum SPF value of 15 or higher and other sun protection measures including: Sun Protection Measures:
- limit time in the sun, especially from 10 a.m. -2 p.m.
- wear long-sleeved shirts, pants, hats and sunglasses.

Other Information:

Protect this product from excessive heat and direct sun.

Inactive Ingredients:

Algae Extract, Aloe Barbadensis Leaf (Aloe Vera Gel) Juice, Benzyl Alcohol, Butyloctyl Salicylate, Butyrospermum Parkii (Shea) Butter, Calendula Officinalis Extract, Camellia Sinensis (Green Tea) Extract, Caprylic/Capric Triglyceride, Cetearyl Alcohol, Citric Acid, Citrullus Lanatus (Watermelon) Extract, Cocos Nucifera (Coconut) Oil, Crambe Maritima (Sea Kale) Extract, Decyl Glucoside, Dehydroacetic Acid, Dodecane, Fucus Vesiculosus (Bladderwrack Seaweed) Extract, Glycerin, Glyceryl Stearate, Helianthus Annuus (Sunflower) Oil, Hydroxyethylcellulose, Lactococcus Ferment Lysate, Natural Fragrance, Persea Gratissima (Avocado) Oil, Polyhydroxystearic Acid, Simmondsia Chinensis (Jojoba) Oil, Propanediol, Sorbitan Stearate, Theobroma Cacao (Cocoa) Butter, Tocopheryl Acetate (Vitamin E), Tridecyl Salicylate, Water, Xanthan Gum.

Questions?

Call toll free 1-877-317-3106